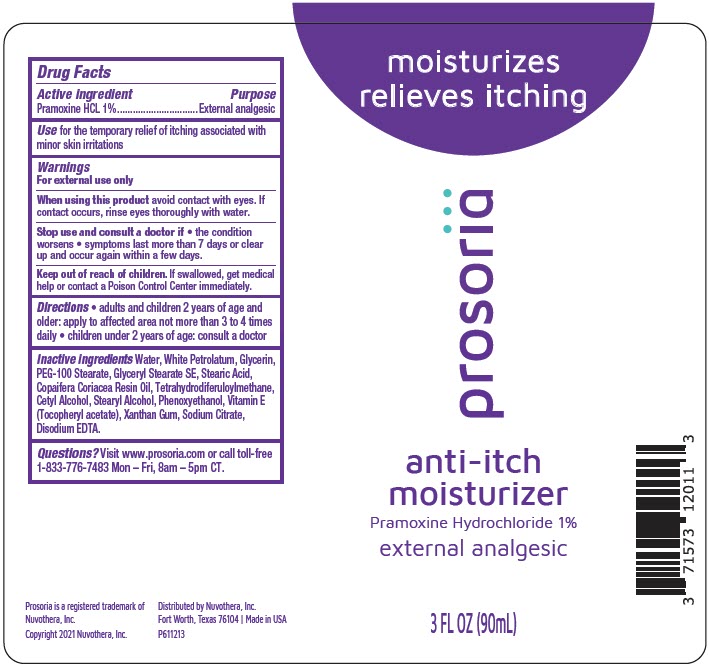 DRUG LABEL: Prosoria Anti-Itch Moisturizer
NDC: 71573-120 | Form: LOTION
Manufacturer: Nuvothera, Inc.
Category: otc | Type: HUMAN OTC DRUG LABEL
Date: 20240110

ACTIVE INGREDIENTS: Pramoxine Hydrochloride 0.9 g/90 mL
INACTIVE INGREDIENTS: Water; Cetyl alcohol; COPAIFERA OFFICINALIS RESIN; Tetrahydrodiferuloylmethane; Glyceryl Stearate SE; PEG-100 STEARATE; Phenoxyethanol; Edetate Disodium Anhydrous; SODIUM CITRATE, UNSPECIFIED FORM; Stearic Acid; Glycerin; Stearyl Alcohol; .ALPHA.-TOCOPHEROL ACETATE; Xanthan Gum

Prosoria Anti-Itch Scalp Moisturizer

Drug Facts

Active ingredient

Pramoxine HCL 1%

Purpose

External analgesic

Use

for the temporary relief of itching associated with minor skin irritations

Warnings

For external use only

When using this product avoid contact with eyes. If contact occurs, rinse eyes thoroughly with water.

Stop use and consult a doctor if

- the condition worsens
- symptoms last more than 7 days or clear up and occur again within a few days.

Keep out of reach of children. If swallowed, get medical help or contact a Poison Control Center immediately.

Directions

- adults and children 2 years of age and older: apply to affected area not more than 3 to 4 times daily
- children under 2 years of age: consult a doctor

Inactive ingredients

Water, White Petrolatum, Glycerin, PEG-100 Stearate, Glyceryl Stearate SE, Stearic Acid, Copaifera Coriacea Resin Oil, Tetrahydrodiferuloylmethane, Cetyl Alcohol, Stearyl Alcohol, Phenoxyethanol, Vitamin E (Tocopheryl acetate), Xanthan Gum, Sodium Citrate, Disodium EDTA.

Questions?

Visit www.prosoria.com or call toll-free 1-833-776-7483 Mon – Fri, 8am – 5pm CT.

Distributed by Nuvothera, Inc.
Fort Worth, Texas 76104

PRINCIPAL DISPLAY PANEL - 90 mL Bottle Label

moisturizes
relieves itching

prosoriä

anti-itch
moisturizer

Pramoxine Hydrochloride 1%

external analgesic

3 FL OZ (90mL)